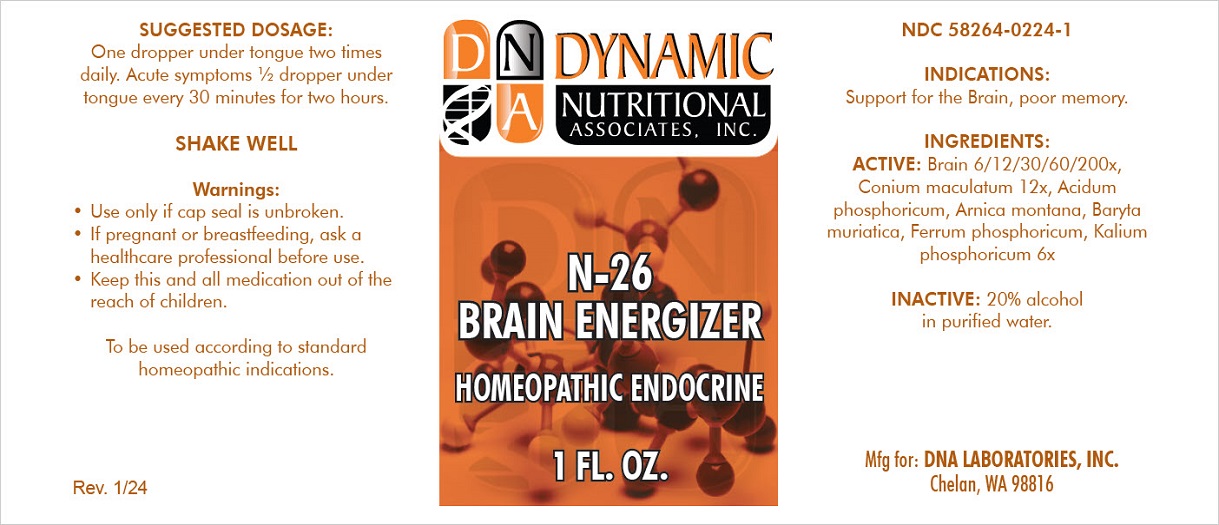 DRUG LABEL: N-26
NDC: 58264-0224 | Form: SOLUTION
Manufacturer: DNA Labs, Inc.
Category: homeopathic | Type: HUMAN OTC DRUG LABEL
Date: 20250109

ACTIVE INGREDIENTS: BARIUM CHLORIDE DIHYDRATE 6 [hp_X]/1 mL; CONIUM MACULATUM WHOLE 12 [hp_X]/1 mL; ARNICA MONTANA 6 [hp_X]/1 mL; PHOSPHORIC ACID 6 [hp_X]/1 mL; DIBASIC POTASSIUM PHOSPHATE 6 [hp_X]/1 mL; FERROSOFERRIC PHOSPHATE 6 [hp_X]/1 mL; PORK BRAIN 200 [hp_X]/1 mL
INACTIVE INGREDIENTS: ALCOHOL; WATER

N-26

NDC 58264-0224-1

INDICATIONS

PURPOSE

Support for the Brain, poor memory.

INGREDIENTS

ACTIVE

Baryta muriatica 6x, Conium maculatum 12x, Arnica montana 6x, Acidum phosphoricum 6x, Kalium phosphoricum 6x, Ferrum phosphoricum 6x, Brain 6/12/30/60/200x

INACTIVE

20% alcohol in purified water.

SUGGESTED DOSAGE

One dropper under tongue two times daily. Acute symptoms ½ dropper under tongue every 30 minutes for two hours.

STORAGE AND HANDLING

SHAKE WELL

Warnings

- Use only if cap seal is unbroken.

PREGNANCY OR BREAST FEEDING

- If pregnant or breastfeeding, ask a healthcare professional before use.

KEEP OUT OF REACH OF CHILDREN

- Keep this and all medication out of the reach of children.

To be used according to standard homeopathic indications.

PRINCIPAL DISPLAY PANEL - 1 FL. OZ. Bottle Label

DYNAMIC
NUTRITIONAL
ASSOCIATES, INC.

N-26
BRAIN ENERGIZER

HOMEOPATHIC ENDOCRINE

1 FL. OZ.